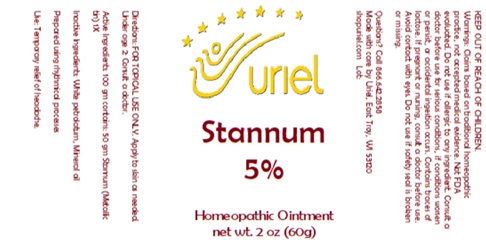 DRUG LABEL: Stannum 5
NDC: 48951-8207 | Form: OINTMENT
Manufacturer: Uriel Pharmacy Inc.
Category: homeopathic | Type: HUMAN OTC DRUG LABEL
Date: 20250107

ACTIVE INGREDIENTS: TIN 1 [hp_X]/1 g
INACTIVE INGREDIENTS: PETROLATUM; MINERAL OIL

Stannum 5

INDICATIONS AND USAGE

Directions: FOR TOPICAL USE ONLY.

DOSAGE AND ADMINISTRATION

Apply to skin as needed. Under age 2: Consult a doctor.

ACTIVE INGREDIENT

Active Ingredients: 100 gm contains: 50 gm Stannum (Metallic tin) 1X

Inactive Ingredients: White petrolatum, Mineral oil

Prepared using rhythmical processes.

PURPOSE

Use: Temporary relief of headache.

KEEP OUT OF REACH OF CHILDREN.

WARNINGS

Warnings: Claims based on traditional homeopathic practice, not accepted medical evidence. Not FDA evaluated. Do not use if allergic to any ingredient. Consult a doctor before use for serious conditions, if conditions worsen or persist, or accidental ingestion occurs. If pregnant or nursing, consult a doctor before use. Avoid contact with eyes. Do not use if safety seal is broken or missing.

QUESTIONS

Questions? Call 866.642.2858 Made with care by Uriel, East Troy, WI 53120 www.urielpharmacy.com